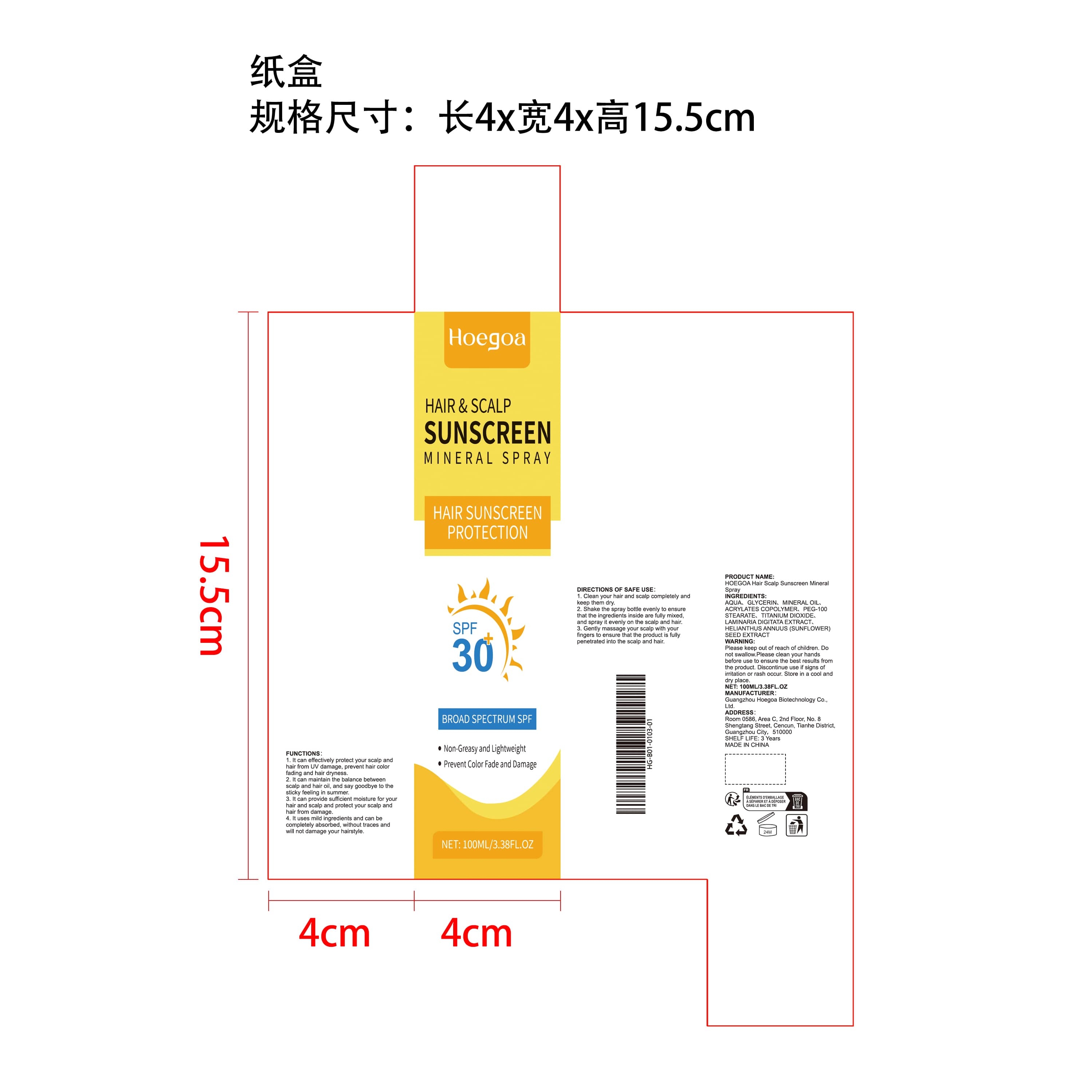 DRUG LABEL: HOEGOA Hair Scalp Sunscreen Mineral
NDC: 85064-019 | Form: LIQUID
Manufacturer: Guangzhou Hoegoa Biotechnology Co., Ltd.
Category: otc | Type: HUMAN OTC DRUG LABEL
Date: 20251128

ACTIVE INGREDIENTS: MINERAL OIL 3 mg/100 mg; LAMINARIA DIGITATA 0.1 mg/100 mg; HELIANTHUS ANNUUS (SUNFLOWER) SEED OIL 0.1 mg/100 mg
INACTIVE INGREDIENTS: PEG-100 STEARATE 2 mg/100 mg; GLYCERIN 3 mg/100 mg; SODIUM ACRYLATES CROSSPOLYMER-2 2 mg/100 mg; TITANIUM DIOXIDE 1 mg/100 mg; AQUA 88.8 mg/100 mg

ACTIVE INGREDIENT

MINERAL OIL、LAMINARIA DIGITATA EXTRACT、HELIANTHUS ANNUUS (SUNFLOWER) SEED EXTRACT

PURPOSE

1. It can effectively protect your scalp and hair from UV damage, prevent hair color fading and hair dryness.

2. It can maintain the balance between scalp and hair oil, and say goodbye to the sticky feeling in summer.

3. It can provide sufficient moisture for your hair and scalp and protect your scalp and hair from damage.

4. It uses mild ingredients and can be completely absorbed, without traces and will not damage your hairstyle.

WHEN USING

1. Clean your hair and scalp completely and keep them dry.

2. Shake the spray bottle evenly to ensure that the ingredients inside are fully mixed, and spray it evenly on the scalp and hair.

3. Gently massage your scalp with your fingers to ensure that the product is fully penetrated into the scalp and hair.

WARNINGS

Please keep out of reach of children. Do not swallow.Please clean your hands before use to ensure the best results from the product. Discontinue use if signs of irritation or rash occur. Store in a cool and dry place.

DO NOT USE

Discontinue use if signs of irritation or rash occur.

STOP USE

Discontinue use if signs of irritation or rash occur.

KEEP OUT OF REACH OF CHILDREN

Please keep out of reach of children. Do not swallow.

STORAGE AND HANDLING

Store in a cool and dry place.

INACTIVE INGREDIENT

AQUA、GLYCERIN、ACRYLATES COPOLYMER、PEG-100 STEARATE、TITANIUM DIOXIDE

INDICATIONS AND USAGE

1. Clean your hair and scalp completely and keep them dry.

2. Shake the spray bottle evenly to ensure that the ingredients inside are fully mixed, and spray it evenly on the scalp and hair.

3. Gently massage your scalp with your fingers to ensure that the product is fully penetrated into the scalp and hair.

DOSAGE AND ADMINISTRATION

1. Clean your hair and scalp completely and keep them dry.

2. Shake the spray bottle evenly to ensure that the ingredients inside are fully mixed, and spray it evenly on the scalp and hair.

3. Gently massage your scalp with your fingers to ensure that the product is fully penetrated into the scalp and hair.